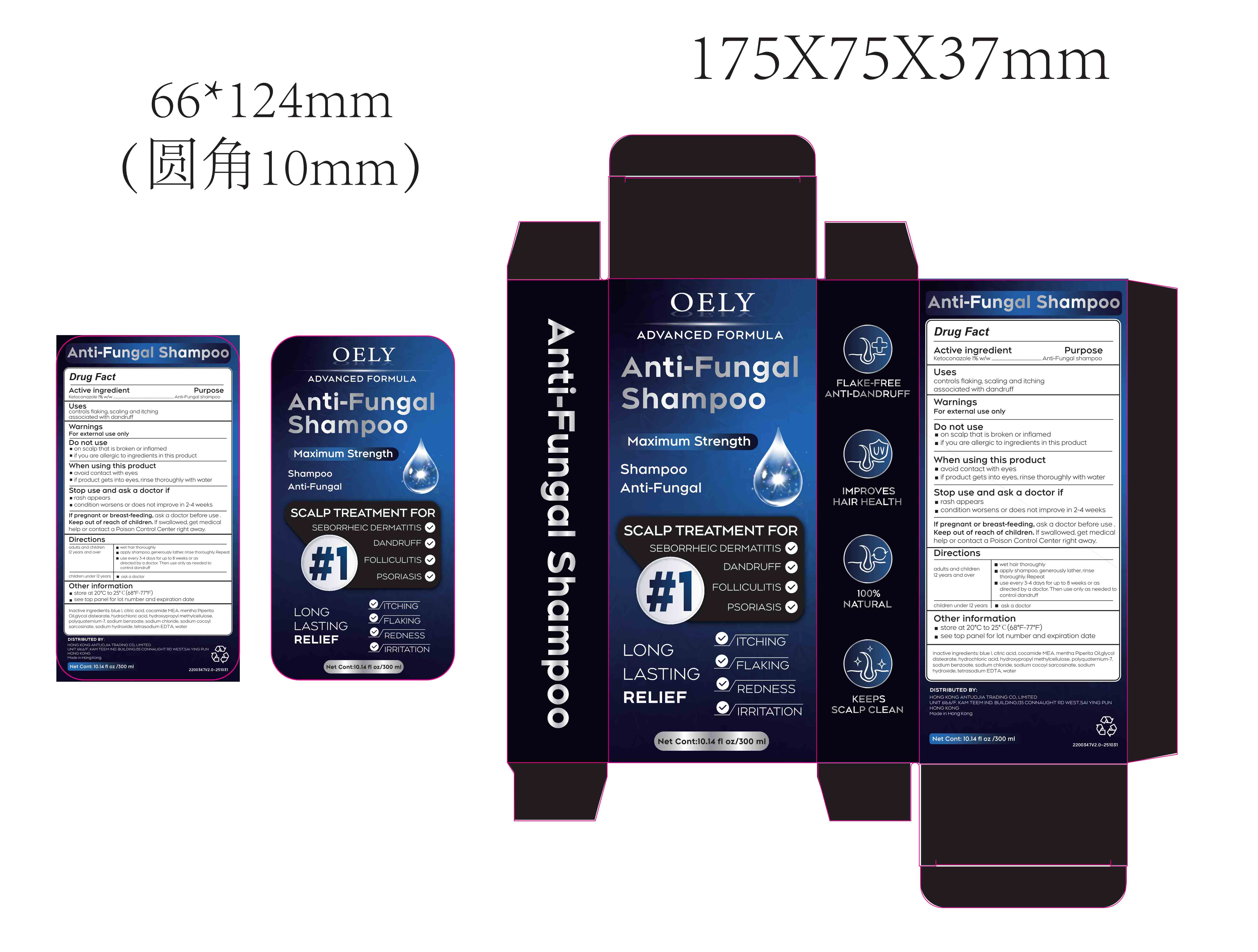 DRUG LABEL: Anti-Fungal
NDC: 87255-008 | Form: SHAMPOO
Manufacturer: Shenzhen Mengyue Technology Co., Ltd.
Category: otc | Type: HUMAN OTC DRUG LABEL
Date: 20260115

ACTIVE INGREDIENTS: KETOCONAZOLE 1 mg/100 mL
INACTIVE INGREDIENTS: HYDROXYPROPYL METHYLCELLULOSE; COCAMIDE MEA; POLYQUATERNIUM-7; SODIUM HYDROXIDE; CITRIC ACID; DISPERSE BLUE 1; HYDROCHLORIC ACID; SODIUM COCOYL SARCOSINATE; TETRASODIUM EDTA; WATER; SODIUM BENZOATE; SODIUM CHLORIDE; MENTHA PIPERITA (PEPPERMINT) OIL; GLYCOL DISTEARATE

87255-008

ACTIVE INGREDIENT

Ketoconazole 1%

PURPOSE

Anti-Fungal shampoo

Uses

controls flaking, scaling and itching associated with dandruff

Warnings

For external use only

Do not use

- on scalp that is broken or inflamed

- if you are allergic to ingredients in this product

When using this product

- avoid contact with eyes

- if product gets into eyes,rinse thoroughly with water

Stop use and ask a doctor if

- rash appears

- condition worsens or does not improve in 2-4 weeks

KEEP OUT OF REACH OF CHILDREN

If pregnant or breast-feeding, ask a doctor before use.

Keep out of reach of children. If swallowed,get medical help or contact a Poison Control Center right away.

Directions

adults and children 12 years and over

- wet hair thoroughly

- apply shampoo, generously lather, rinse thoroughly.Repeat

- use every 3-4 days for up to 8 weeks or as directed by a doctor.Then use only as needed to control dandruff

children under 12 years

- ask a doctor

Other information

- store at 20℃ to 25℃(68°F-77°F)

- see top panel for lot number and expiration date

Inactive ingredients

blue l, citric acid, cocamide MEA. mentha Piperita Oil.glycol distearate, hydrochloric acid, hydroxypropyl methylcellulose, polyquaternium-7.sodium benzoate, sodium chloride, sodium cocoyl sarcosinate, sodium hydroxide, tetrasodium EDTA, water